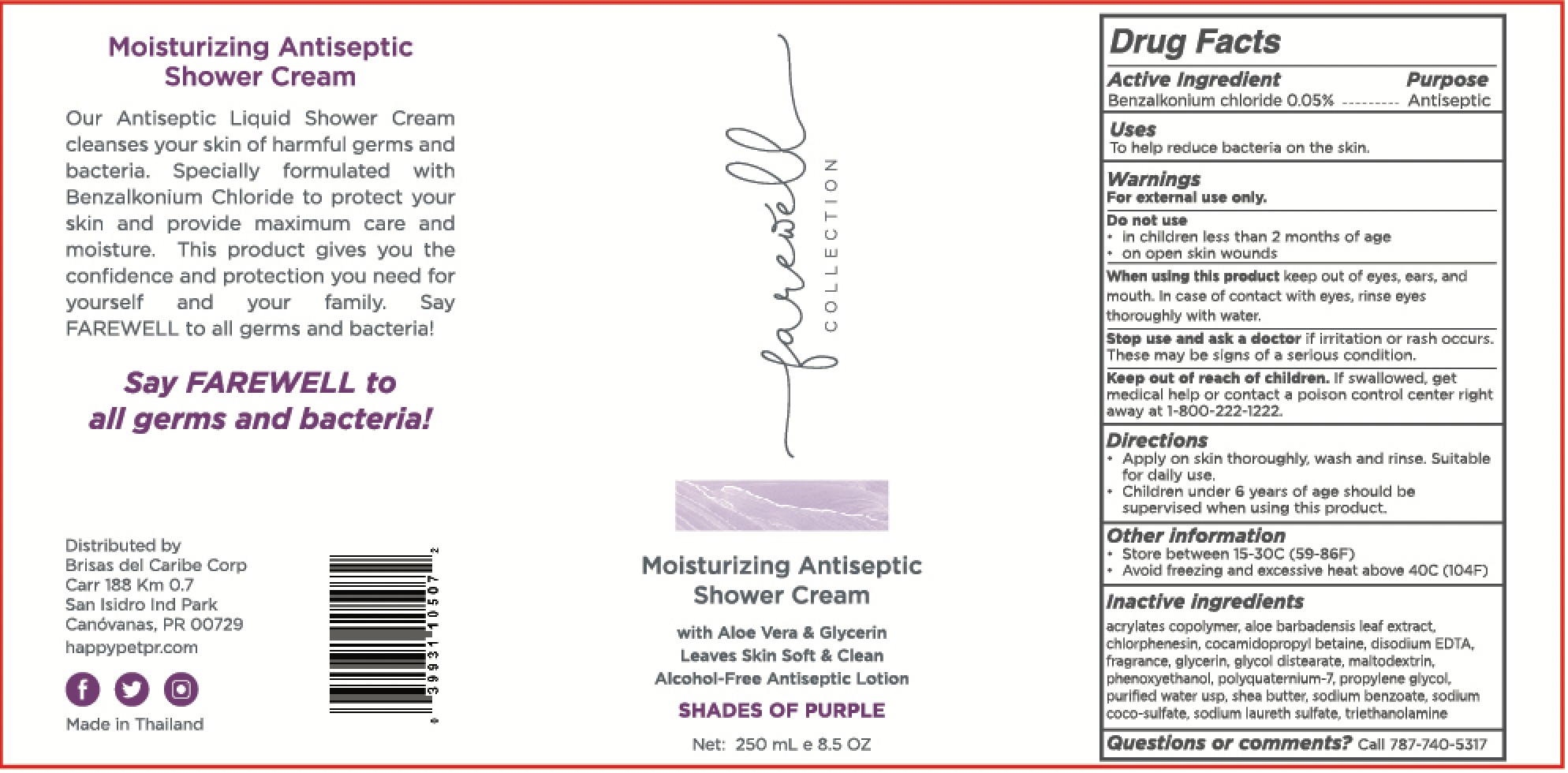 DRUG LABEL: Farewell Collection
NDC: 12961-114 | Form: CREAM
Manufacturer: Brisas del Caribe Corp.	
Category: otc | Type: HUMAN OTC DRUG LABEL
Date: 20221214

ACTIVE INGREDIENTS: BENZALKONIUM CHLORIDE 0.05 mg/100 mL
INACTIVE INGREDIENTS: SODIUM LAURYL SULFATE; PHENOXYETHANOL; CHLORPHENESIN; GLYCERIN; WATER; TROLAMINE; SODIUM COCO-SULFATE; POLYQUATERNIUM-7 (70/30 ACRYLAMIDE/DADMAC; 1600 KD); ALOE VERA LEAF; PROPYLENE GLYCOL; GLYCOL DISTEARATE; COCAMIDOPROPYL BETAINE; ACRYLATES CROSSPOLYMER-6; EDETATE DISODIUM ANHYDROUS; SODIUM BENZOATE; SHEA BUTTER; MALTODEXTRIN

Brisas-Paveemol Shower Cream Purple Label

Active Ingredient(s)

Benzalkonium chloride 0.05 %.

Purpose

Antiseptic

Use

To help reduce bacteria on hands.

Warnings

For external use only.

Do not use

- in children less than 2 months of age
- on open skin wounds

When using this product keep out of eyes, ears, and mouth. In case of contact with eyes, rinse eyes thoroughly with water.
Stop use and ask a doctor if irritation or rash occurs. These may be signs of a serious condition.
Keep out of reach of children. If swallowed, get medical help or contact a Poison Control Center right away.

Stop use and ask a doctor if irritation or rash occurs. These may be signs of a serious condition.

Keep out of reach of children. If swallowed, get medical help or contact a Poison Control Center right away 1 800-222-1222

Directions

- Apply on skin thoroughly, wash, and rinse. Suitable to daily use.
- Supervise children under 6 years of age when using this product to avoid swallowing.

Other information

- Store between 15 and 30C (59-86F)
- Avoid freezing and excessive heat above 40C (104F)

Inactive ingredients

acrylates copolymer, aloe barbadensis leaf extract, chlorphenesin, cocamidopropyl betaine, disodium EDTA, glycerin, glycol distearate, maltodextrin, phenoxyethanol, polyquaternium-7, propylene glycol, purified water USP, shea butter, sodium benzoate, sodium coco-sulfate, sodium laureth sulfate, triethanolamine.

Package Label - Principal Display Panel

250 mL NDC : 12961-114-11